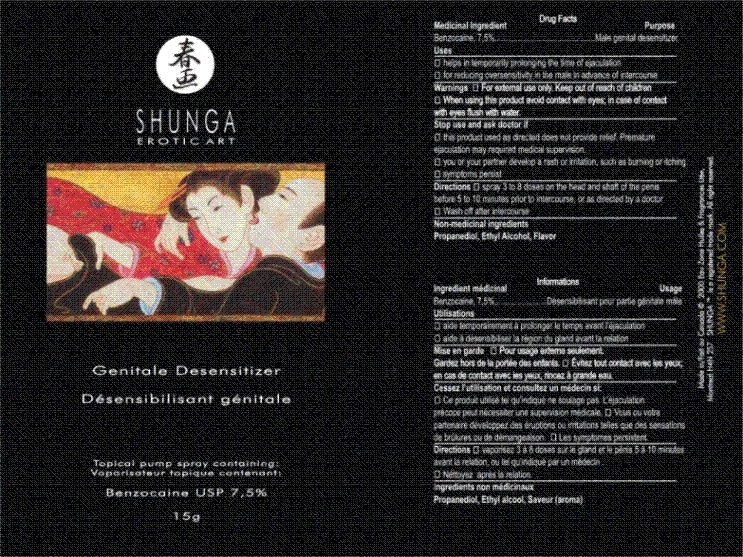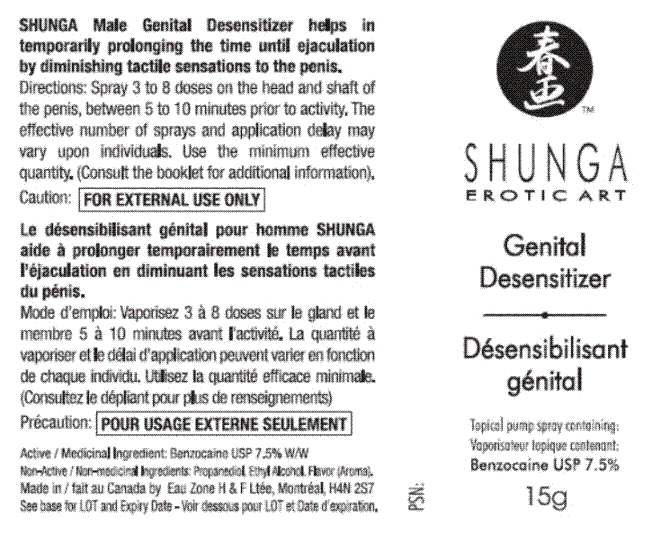 DRUG LABEL: Shunga
NDC: 63240-5100 | Form: AEROSOL, SPRAY
Manufacturer: Eau Zone Oils & Fragrances LTD
Category: otc | Type: HUMAN OTC DRUG LABEL
Date: 20221109

ACTIVE INGREDIENTS: BENZOCAINE 1.125 g/15 g
INACTIVE INGREDIENTS: PROPYLENE GLYCOL 9.375 g/15 g; ALCOHOL 4.35 g/15 g

Drug Facts

Active Ingredient
Topical Pump Spray
Benzocaine 7.5 pourcentage
7.0 mg per spray

Genital Desensitizer
Désensibilisant Genital
Topical pump spray containing:
Vaporisateur topique contenant:
Benzocaine USP 7.5 pourcent
15g

Stop use and ask doctor if
This product used as directed does not provide relief. Premature ejaculation may require medical supervision.
You or your partner develops a rash or irritation, such as burning or itching.
Symptoms persist

Warnings
FOR EXTERNAL USE ONLY. Keep out of reach of children
When using this product, avoid contact with eyes; in case of contact with eyes, flush with water.
Do not inhale.
Do not exceed a maximum of 24 sprays in 24 hours.

PURPOSE

Name: SHUNGA Genital Desensitizer

SHUNGA Male Genital Desensitizer helps in temporarily prolonging the time until ejaculation by diminishing tactile sensations to the penis.
Directions: Spray 3 to 8 doses on the head and shaft of the penis, between 5 to 10 minutes prior to activity. The effective number of sprays and application delay may vary upon individuals. Use the minimum effective quantity. (Consult the booklet for additional information).
Purpose
Male genital desensitizer
Uses
It helps in temporarily prolonging the time until ejaculation by diminishing tactile sensations to the penis. Use for reducing oversensitivity in advance of intercourse.
Directions
Spray 3 to 8 doses on the head and shaft of the penis, between 5 to 15 minutes prior to intercourse. The effective number of sprays and application delay may vary upon individuals. Use the minimum effective quantity. Wash off after intercourse.
Other information
Store below 25ºC (77ºF). Each spray application contains 7.0 mg of Benzocaine and there are about 170 spray doses per container.

Inactive ingredients
PROPANEDIOL, ETHYL ALCOHOL, FLAVOR (AROMA)
Poids net/Net W. 15 g

Made in Canada by Eau Zone H and F Ltée, Montreal, H4N 2S7
See base for LOT and Expiry Date

Directions

Spray 3 to 8 doses on the head and shaft of the penis, between 5 to 10 minutes prior to intercourse. The effective number of sprays and application delay may vary upon individuals. Use the minimum effective quantity. Wash off after intercourse.

Warnings

FOR EXTERNAL USE ONLY

When using this product. Avoid contact with eyes; in case of contact with eyes flush with water. Do not exceed a maximum of 24 sprays in 24 hours. Do not inhale.Do not use in large quantities or on large body surface. Do not use in case of allergy to benzocaine or to any ingredient contained in this product.

Uses

It helps in temporarily prolonging the time until ejaculation by diminishing tactile sensations to the penis. Use for reducing oversensitivity in advance of intercourse.

PACKAGE LABEL

<paragraph>

PACKAGE LABEL

PD3